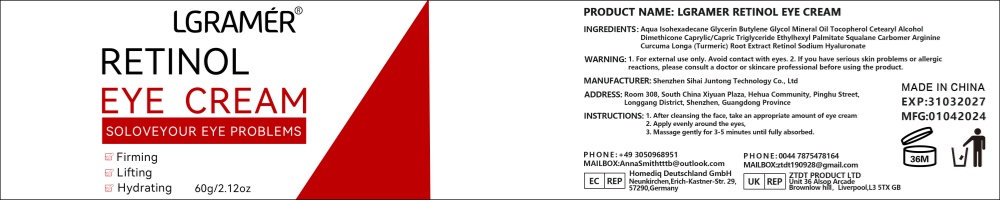 DRUG LABEL: LGRAMERRETINOLEYECREAM
NDC: 84350-003 | Form: CREAM
Manufacturer: Shenzhen Sihai Juntong Technology Co., Ltd
Category: otc | Type: HUMAN OTC DRUG LABEL
Date: 20240801

ACTIVE INGREDIENTS: SQUALANE 1 g/100 mg
INACTIVE INGREDIENTS: WATER

ACTIVE INGREDIENT

Squalane 10%

INACTIVE INGREDIENT

Water 5%

PURPOSE

Firms and moisturizes

WARNINGS

WARNING: 1.For external use only.Avoid contact with eyes.2.If you have serious skin problems or allergic react
before using the product.

Do not use

If you have allergic reactions, stop to use

WHEN USING

1. After cleansing the face, take an appropriate amount of eye cream
2. Apply evenly around the eyes,
3. Massage gently for 3-5 minutes until fully absorbed.

Keep out of reach of children

Dosage and administration

appropriate amount

INDICATIONS AND USAGE

INSTRUCTIONS: 1. After deansing the face, take an appropriate amount of eye cream2. Apply evenly around the eyes,3. Massage gently for 3-5 minutes until fully absorbed.

PACKAGE LABEL

60g NDC.84350-003-01